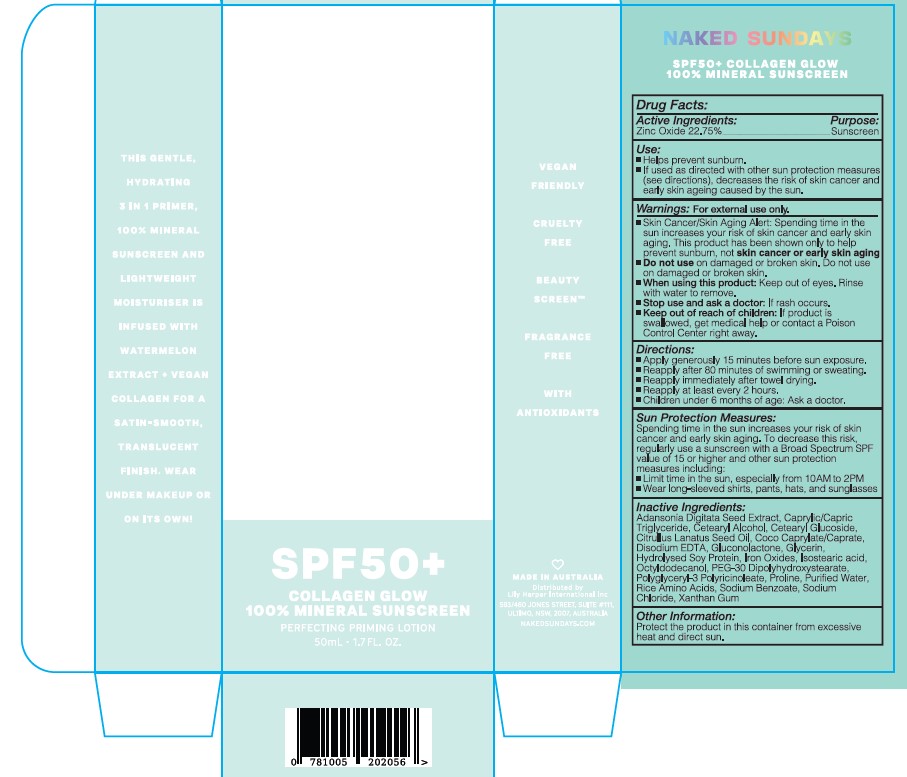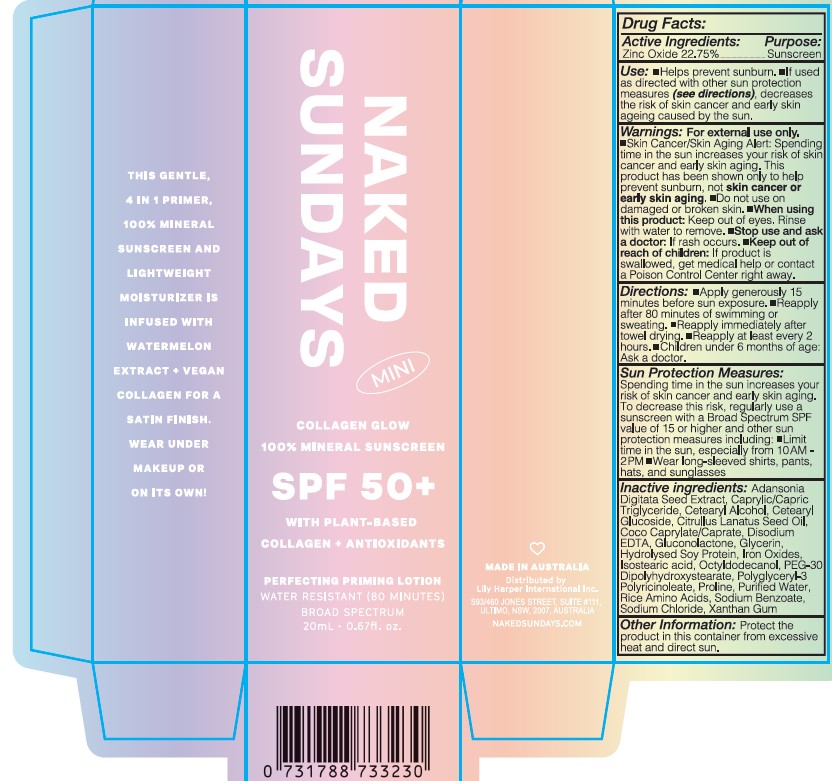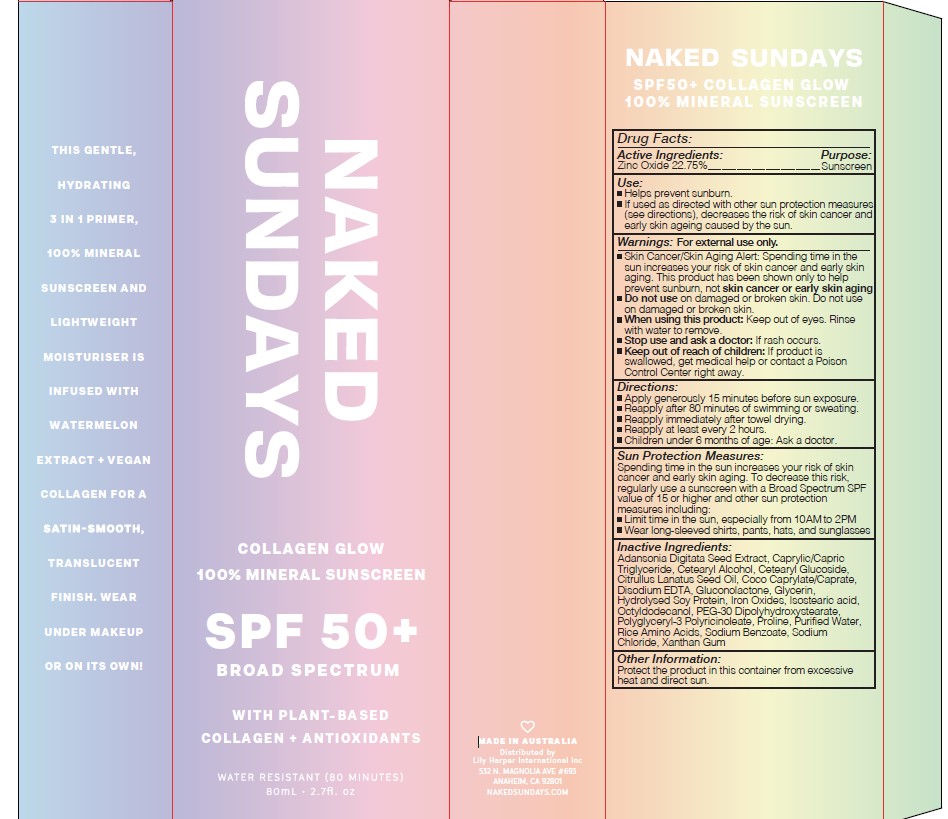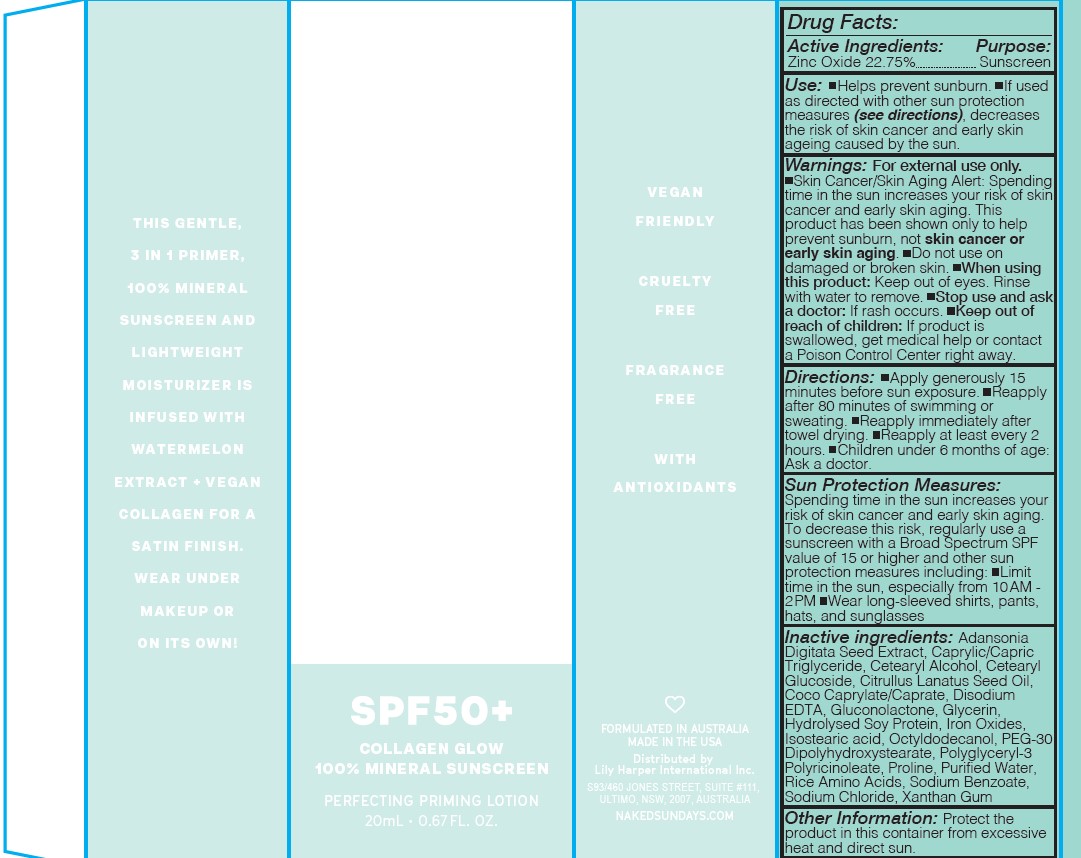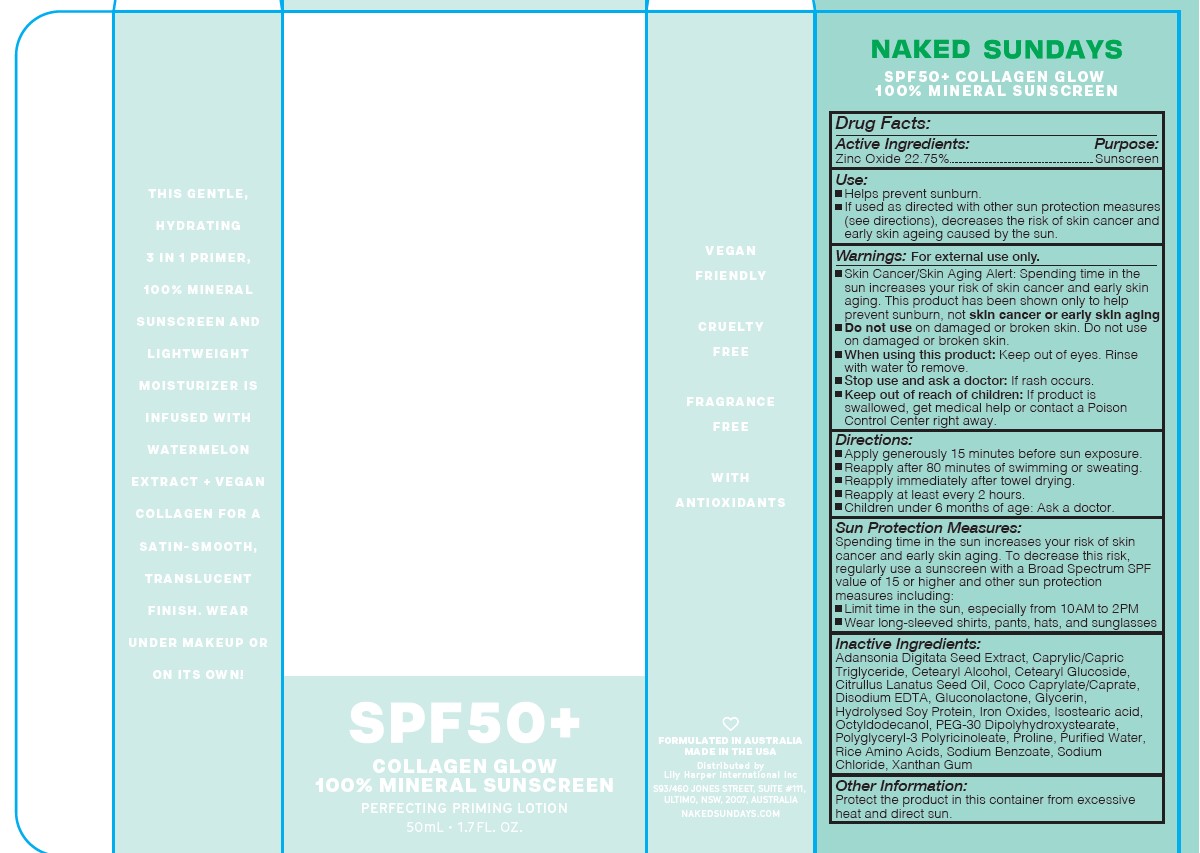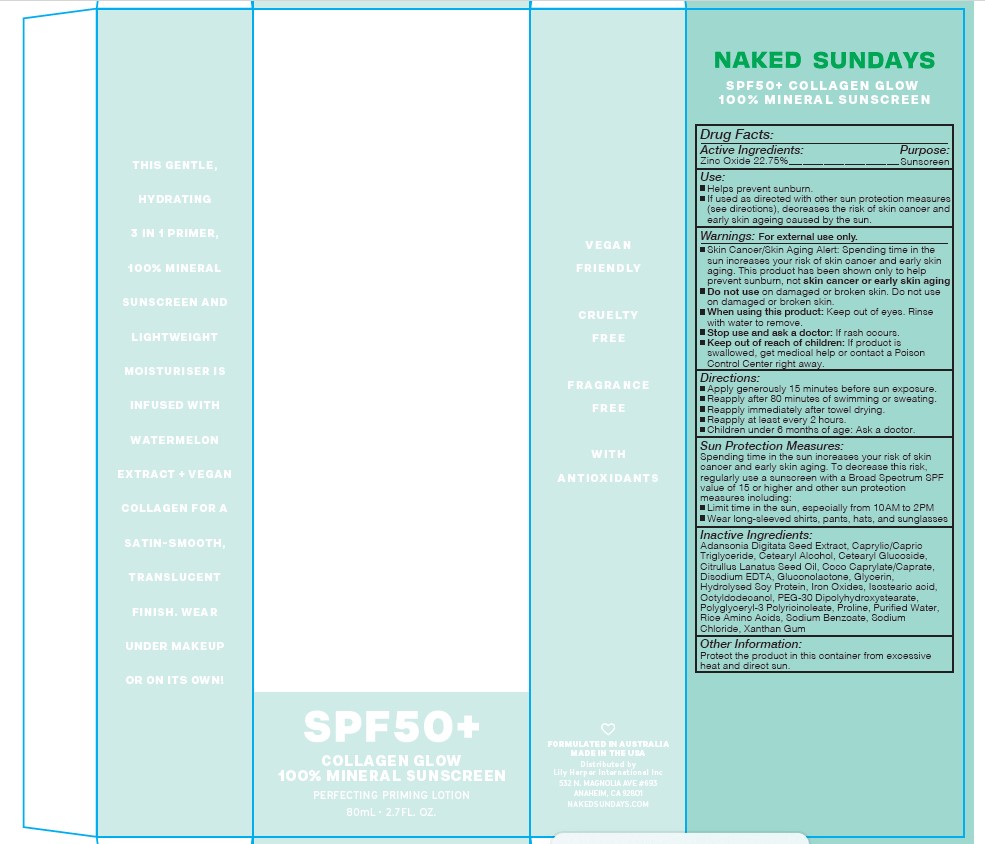 DRUG LABEL: COLLAGEN GLOW MINERAL SUNSCREEN
NDC: 81104-103 | Form: LOTION
Manufacturer: NAKED SUNDAYS PTY LTD
Category: otc | Type: HUMAN OTC DRUG LABEL
Date: 20250623

ACTIVE INGREDIENTS: ZINC OXIDE 22.75 g/100 mL
INACTIVE INGREDIENTS: CETEARYL GLUCOSIDE; CETOSTEARYL ALCOHOL; COCO-CAPRYLATE; EDETATE DISODIUM; GLUCONOLACTONE; ADANSONIA DIGITATA SEED; ORYZA SATIVA WHOLE; HYDROLYZED SOY PROTEIN (ENZYMATIC; 2000 MW); ISOSTEARIC ACID; TRICAPRIN; OCTYLDODECANOL; PEG-30 DIPOLYHYDROXYSTEARATE; POLYGLYCERYL-3 RICINOLEATE; PROLINE; WATER; SODIUM BENZOATE; SODIUM CHLORIDE

NAKED SUNDAYS COLLAGEN GLOW MINERAL SUNSCREEN LOTION SPF 50

ACTIVE INGREDIENT

ZINC OXIDE 22.75%

Purpose

Sunscreen

USES

- Helps prevent sunburn.
- If used as directed with other sun protection measures (see directions), decreases the risk of skin cancer and early skin ageing caused by the sun.

WARNINGS

For external use only.

- Do not use on damaged or broken skin.
- When using this product: keep out of eyes. Rinse with water to remove.
- Stop use and ask a doctor if: rash occurs.

- CONTAINS SODIUM BENZOATE.

Keep out of reach of children. If product is swallowed, get medical help or contact a Poison Control Center right away.

DIRECTIONS

- APPLY GENEROUSLY 15 MINUTES BEFORE SUN EXPOSURE.
- Reapply after 80 minutes of swimming or sweating.
- Reapply immediately after towel drying.
- Reapply at least every 2 hours.
- Children under 3 years of age: Ask a doctor.

SUN PROTECTION MEASURES:

Spending time in the sun increases your risk of skin cancer and early skin aging. To decrease this risk, regularly use a sunscreen with a Broad Spectrum SPF value of 15 or higher and other sun protection measures including:

- Limit time in the sun, especially from 10.00AM - 2.00PM
- Wear long-sleeved shirts, pants, hats, and sunglasses

INACTIVE INGREDIENTS

CETEARYL GLUCOSIDE, CETOSTEARYL ALCOHOL, COCO-CAPRYLATE, DISODIUM EDETATE, GLUCONOLACTONE, HYDROLYZED ADANSONIA DIGITATA SEED EXTRACT, HYDROLYZED RICE PROTEIN, HYDROLYZED SOY PROTEIN, ISOSTEARIC ACID, CAPRIC TRIGLYCERIDES, OCTYLDODECANOL, PEG-30 DIPOLYHYDROXYSTEARATE, POLYGLYCERYL-3 POLYRICINOLEATE, PROLINE, WATER (AQUA), SODIUM BENZOATE, SODIUM CHLORIDE.

OTHER INFORMATION

Protect the product in this container from excessive heat and direct sun.